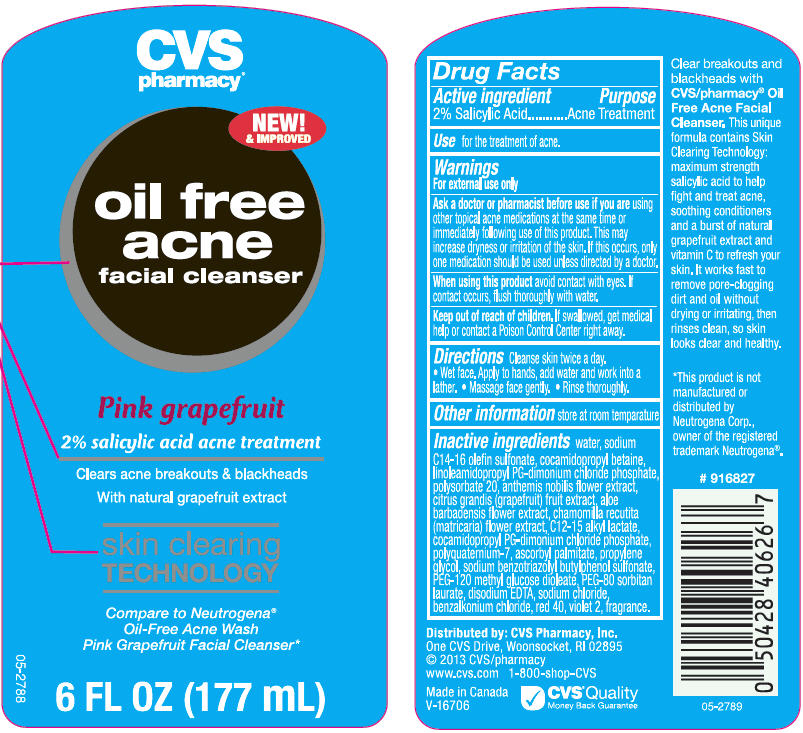 DRUG LABEL: CVS Oil Free Acne Facial Cleanser-Pink Grapefruit 
NDC: 69842-456 | Form: LOTION
Manufacturer: CVS Health
Category: otc | Type: HUMAN OTC DRUG LABEL
Date: 20220125

ACTIVE INGREDIENTS: Salicylic Acid 20 mg/1 mL
INACTIVE INGREDIENTS: Water; Sodium C14-16 Olefin Sulfonate; Cocamidopropyl Betaine; Linoleamidopropyl Propylene Glycol-Dimonium Chloride Phosphate; Polysorbate 20; Chamaemelum Nobile Flower; Pummelo; Aloe Vera Flower; Chamomile; C12-15 Alkyl Lactate; Cocamidopropyl Propylene Glycol-Dimonium Chloride Phosphate; Polyquaternium-7 (70/30 Acrylamide/dadmac; 1600000 MW); Ascorbyl Palmitate; Propylene Glycol; Sodium Benzotriazolyl Butylphenol Sulfonate; PEG-120 Methyl Glucose Dioleate; PEG-80 Sorbitan Laurate; Edetate Disodium; Sodium Chloride; Benzalkonium Chloride; FD&C Red No. 40; D&C Violet No. 2

CVS Oil Free Acne Facial Cleanser-Pink Grapefruit
Acne Treatment

Active ingredients

Salicylic Acid 2.0%

Purpose

Acne Treatment

Use

For the treatment of acne

Warnings

For external use only

Ask a doctor or pharmacist before use if you are using other topical acne medications at the same time or immediately following use of this product. This may increase dryness or irritation of the skin. If this occurs, only one medication should be used unless directed by a doctor.

When using this product avoid contact with eyes. If contact occurs, flush thoroughly with water.

Keep out of reach of children. If swallowed, get medical help or contact a Poison Control Center right away.

Directions

Cleanse skin twice a day

♦ Wet face. Apply to hands, add water and work into a lather.
♦ Massage face gently.
♦ Rinse thoroughly.

Other information

store at room temperature

Inactive ingredients

Water, Sodium C14-16 Olefin Sulfonate, Cocamidopropyl Betaine, Linoleamidopropyl PG-Dimonium Chloride Phosphate, Polysorbate 20, Anthemis Nobilis Flower Extract, Citrus Grandis (Grapefruit) Fruit Extract, Aloe Barbadensis Flower Extract, Chamomilla Recutita (Matriarca) Flower Extract, C12-15 Alkyl Lactate, Cocamidopropyl PG-diamonium Chloride Phosphate, Polyquaternium-7, Ascorbyl Palmitate, Propylene Glycol, Sodium Benzotriazolyl Butylphenol Sulfonate, PEG-120 Methyl Glucose Dioleate, PG-80 Sorbitan Laurate, Disodium EDTA, Sodium Chloride, Benzalkonium Chloride, Red 40, Violet 2, Fragrance.

Distributed by: CVS Pharmacy, Inc.
One CVS Drive, Woonsocket, RI 02895

PRINCIPAL DISPLAY PANEL - 177 mL Bottle Label

CVS
pharmacy®

NEW!
& IMPROVED

oil free
acne
facial cleanser

Pink grapefruit
2% salicylic acid acne treatment

Clears acne breakouts & blackheads
With natural grapefruit extract

skin clearing
TECHNOLOGY

Compare to Neutrogena®
Oil-Free Acne Wash
Pink Grapefruit Facial Cleanser*

6 FL OZ (177 mL)

05-2788